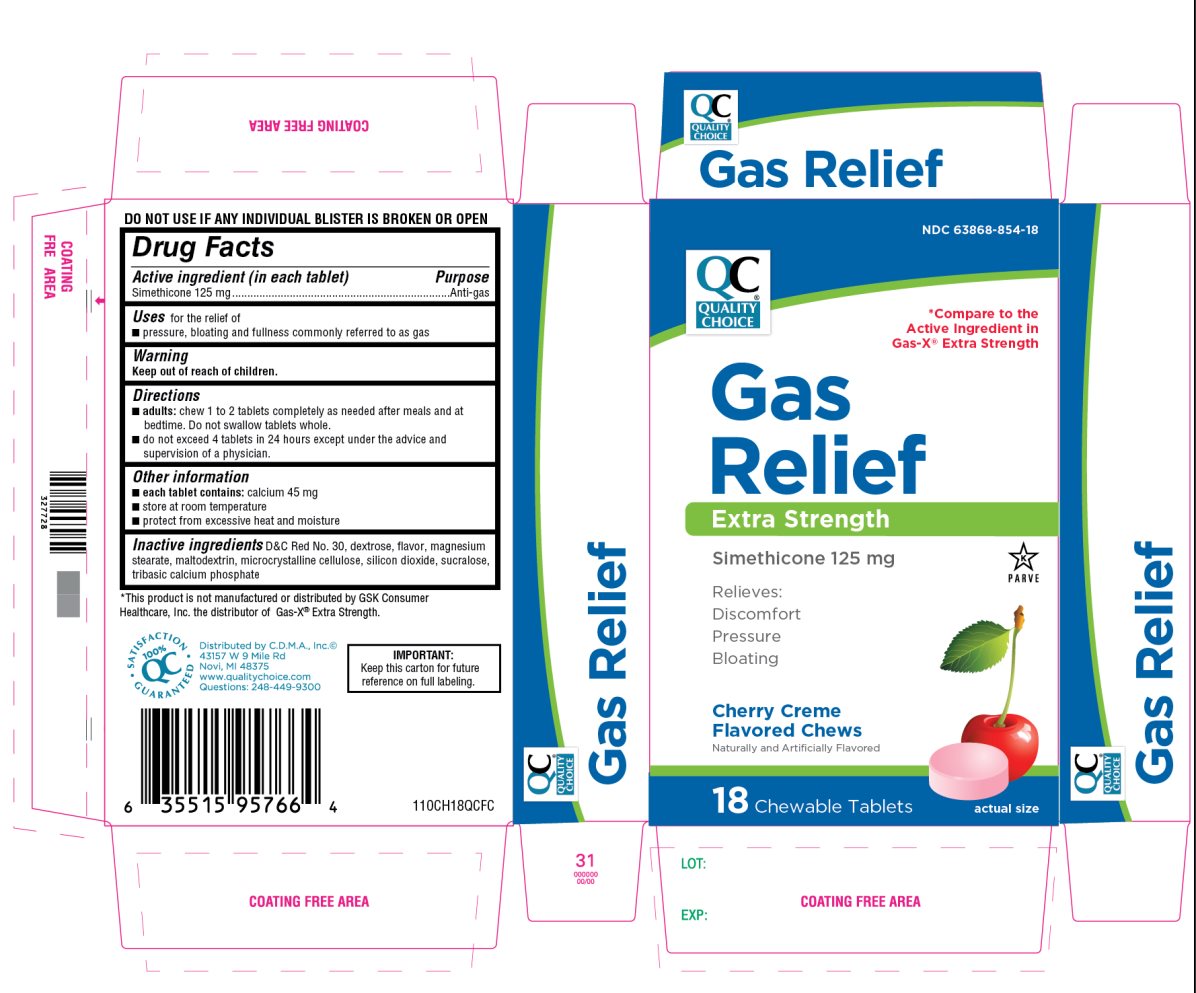 DRUG LABEL: extra strength gas relief
NDC: 63868-854 | Form: TABLET, CHEWABLE
Manufacturer: QUALITY CHOICE (CHAIN DRUG MARKETING ASSOCIATION)
Category: otc | Type: HUMAN OTC DRUG LABEL
Date: 20210121

ACTIVE INGREDIENTS: DIMETHICONE 125 mg/1 1
INACTIVE INGREDIENTS: D&C RED NO. 30; DEXTROSE, UNSPECIFIED FORM; MAGNESIUM STEARATE; MALTODEXTRIN; MICROCRYSTALLINE CELLULOSE; SILICON DIOXIDE; SUCRALOSE; TRIBASIC CALCIUM PHOSPHATE

QUALITY CHOICE Extra Strength Gas Relief

Active ingredient (in each tablet)

Simethicone 125 mg

Purpose

Anti-gas

Uses

For the relief of

- Pressure, bloating and fullness commonly referred to as gas

Directions

- adults: chew 1 to 2 tablets completely as needed after meals and at bedtime. Do not swallow tablets whole.
- do not exceed 4 tablets in a 24 hour period except under the advice and supervision of a physician.

Other information

- each tablets contains: calcium 45 mg
- store at room temperature
- protect from excessive heat and moisture

DO NOT USE IF ANY INDVIDUAL BLISTER IS BROKEN OR OPEN

Inactive ingredients

D & C Red No. 30, dextrose, flavor, magnesium stearate, maltodextrin, microcrystalline cellulose, silicon dioxide, sucralose, tribasic calcium phosphate

Principal Display Panel

QC® QUALITY CHOICE

NDC 63868-854-18

*Compare to the Active Ingredient in Gas-X® Extra Strength

Gas Relief

Extra Strength, Simethicone 125 mg

Relieves:

Discomfort

Pressure

Bloating

Cherry Creme Flavored Chews

Naturally and Artificially Flavored

*This product is not manufactured or distributed by GSK Consumer Healthcare, Inc. the distributor of Gas-X® Extra strength.

100% QC SATISFACTION GURANTEED

Distributed by C.D.M.A., Inc.© 43157 W 9 Mile Rd Novi, MI 48375

www.qualitychoice.com

Questions: 248-449-9300